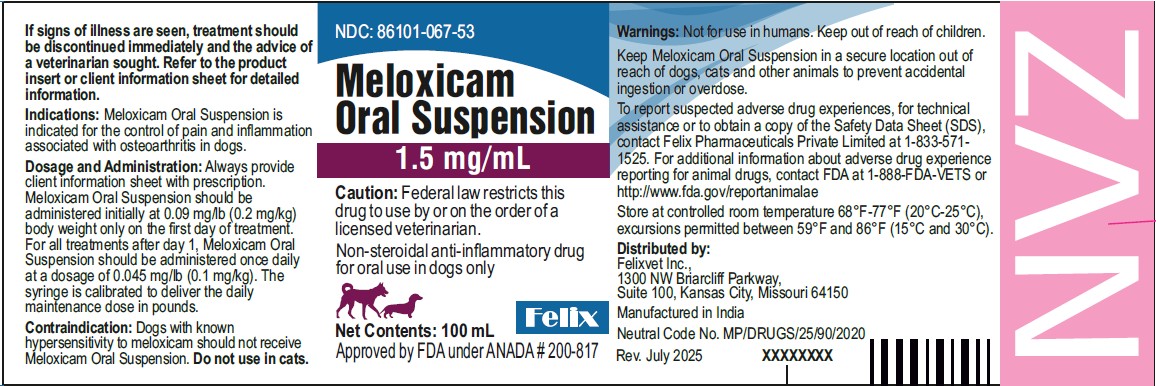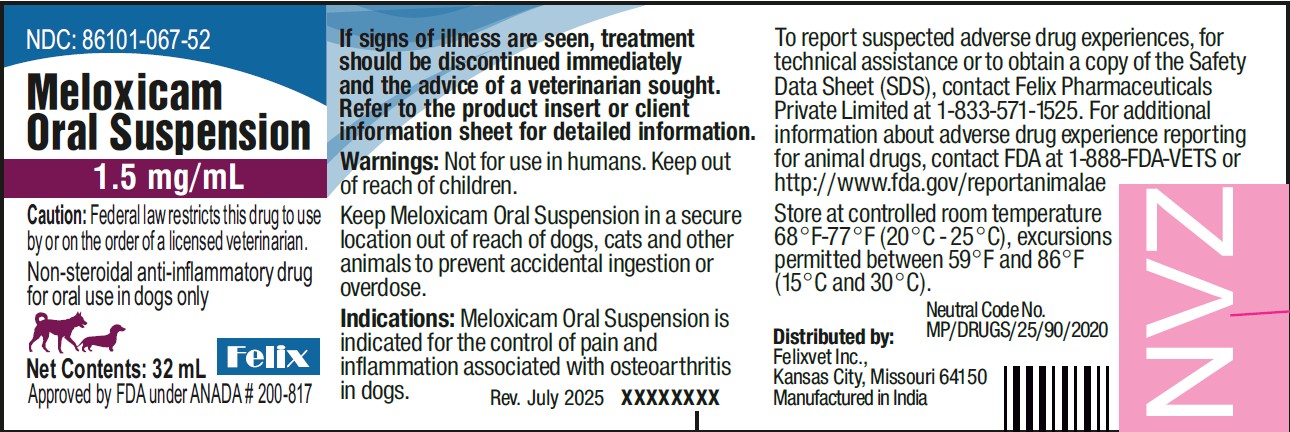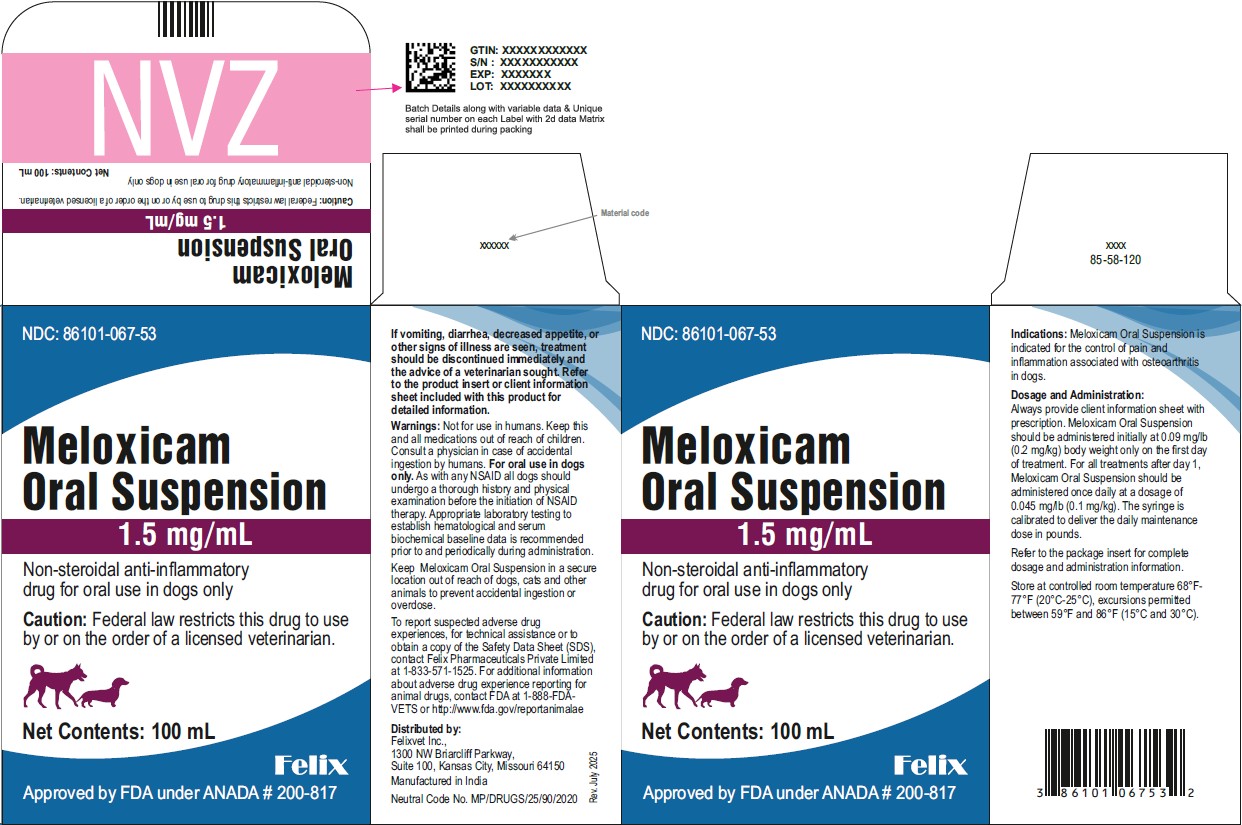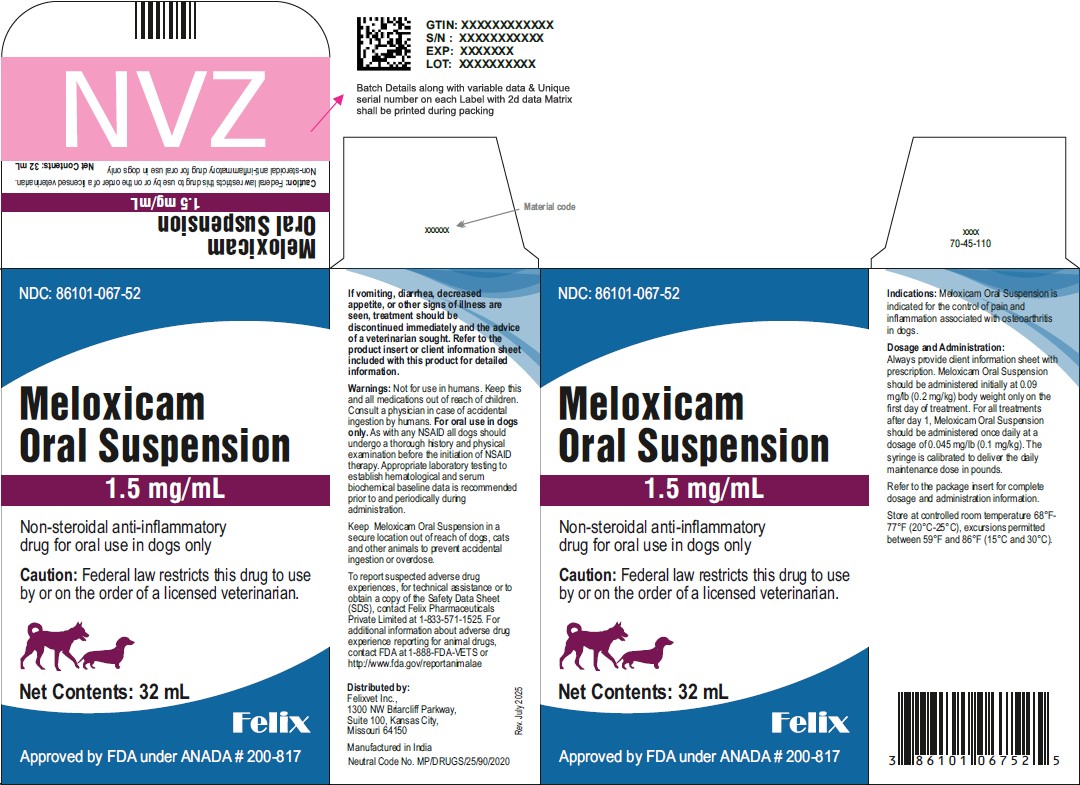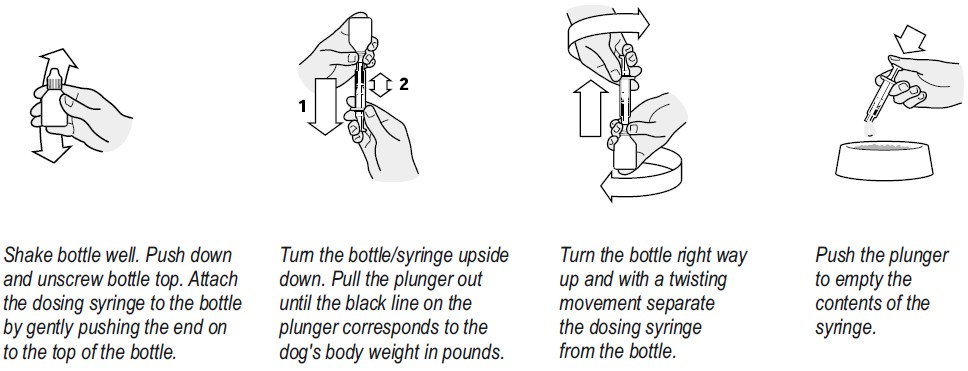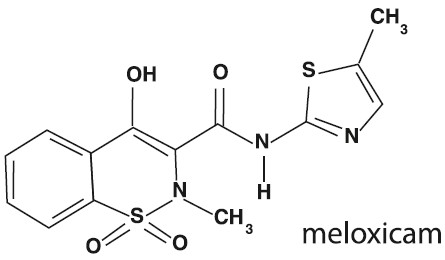 DRUG LABEL: Meloxicam
NDC: 86101-067 | Form: SUSPENSION
Manufacturer: FELIX PHARMACEUTICALS PRIVATE LIMITED
Category: animal | Type: Prescription Animal Drug Label
Date: 20250806

ACTIVE INGREDIENTS: MELOXICAM 1.5 mg/1 mL

Meloxicam Oral Suspension
1.5 mg/mL
(equivalent to 0.05 mg per drop)
Non-steroidal anti-inflammatory drug for oral use in dogs only

Caution:

Federal law restricts this drug to use by or on the order of a licensed veterinarian.

Warning:

Repeated use of meloxicam in cats has been associated with acute renal failure and death. Do not administer additional injectable or oral meloxicam to cats. See Contraindications, Warnings, and Precautions for detailed information.

Description:

Meloxicam is a non-steroidal anti-inflammatory drug (NSAID) of the oxicam class. Each milliliter of Meloxicam Oral Suspension contains meloxicam equivalent to 1.5 milligrams and sodium benzoate (1.5 milligrams) as a preservative. The chemical name for Meloxicam is 4-Hydroxy-2-methyl-N-(5-methyl-2-thiazolyl)-2H-1,2-benzothiazine-3-carboxamide-1, 1-dioxide. The formulation is a yellowish viscous suspension.

Indications:

Meloxicam Oral Suspension is indicated for the control of pain and inflammation associated with osteoarthritis in dogs.

Dosage and Administration:

Always provide client information sheet with prescription. Carefully consider the potential benefits and risk of Meloxicam Oral Suspension and other treatment options before deciding to use Meloxicam Oral Suspension. Use the lowest effective dose for the shortest duration consistent with individual response. Meloxicam Oral Suspension should be administered initially at 0.09 mg/lb (0.2 mg/kg) body weight only on the first day of treatment. For all treatments after day 1, Meloxicam Oral Suspension should be administered once daily at a dose of 0.045 mg/lb (0.1 mg/kg). The syringe is calibrated to deliver the daily maintenance dose in pounds.

Directions for Administration:

Dogs under 10 pounds (4.5 kg)

Shake well before use, then remove cap. Particular care should be given with regard to the accuracy of dosing. To prevent accidental overdosing of small dogs, administer drops on food only, never directly into the mouth. Carefully measure suspension onto food to assure that the correct dose is given before presentation of the food to the dog. The syringe provided with the meloxicam concentration of 1.5 mg/mL cannot be used to measure doses for dogs weighing less than 5 lbs (2.3 kg).

For dogs less than 5 lbs (2.3 kg), Meloxicam Oral Suspension can be given using the dropper bottle: one drop for each pound of body weight for the 1.5 mg/mL concentration (two drops for each kilogram of body weight), dropped directly onto the food.

For dogs between 5-10 pounds, Meloxicam Oral Suspension can be given by drops or by using the measuring syringe provided in the package (see dosing procedure below). The syringe fits on to the bottle and has a scale beginning at 5 lbs, designed to deliver the daily maintenance dose (0.05 mg/lb or 0.1 mg/kg). When using the syringe, the dog's weight should be rounded down to the nearest 5 pound increment. Replace and tighten cap after use.

Dogs over 10 pounds (4.5 kg)

Shake well before use then remove cap. Meloxicam Oral Suspension may be either mixed with food or placed directly into the mouth. Particular care should be given with regard to the accuracy of dosing. Meloxicam Oral Suspension can be given using the measuring syringe provided in the package (see dosing procedure below). The syringe fits on to the bottle and has a scale in pounds designed to deliver the daily maintenance dose (0.05 mg/lb or 0.1 mg/kg). When using the syringe, the dog's weight should be rounded down to the nearest 5 pound increment. Alternatively, Meloxicam Oral Suspension can be given using the dropper bottle: one drop for each pound of body weight for the 1.5 mg/mL concentration (two drops for each kilogram of body weight). Replace and tighten cap after use.

Contraindications:

Dogs with known hypersensitivity to meloxicam should not receive Meloxicam Oral Suspension. Do not use Meloxicam Oral Suspension in cats. Acute renal failure and death have been associated with the use of meloxicam in cats.

Warnings:

Not for use in humans. Keep this and all medications out of reach of children. Consult a physician in case of accidental ingestion by humans. For oral use in dogs only.

As with any NSAID all dogs should undergo a thorough history and physical examination before the initiation of NSAID therapy. Appropriate laboratory testing to establish hematological and serum biochemical baseline data is recommended prior to and periodically during administration. Owner should be advised to observe their dog for signs of potential drug toxicity and be given a client information sheet about Meloxicam Oral Suspension.

Keep Meloxicam Oral Suspension in a secure location out of reach of dogs, cats and other animals to prevent accidental ingestion or overdose.

Precautions:

The safe use of Meloxicam Oral Suspension in dogs younger than 6 months of age, dogs used for breeding, or in pregnant or lactating dogs has not been evaluated. Meloxicam is not recommended for use in dogs with bleeding disorders, as safety has not been established in dogs with these disorders. As a class, cyclo-oxygenase inhibitory NSAIDs may be associated with gastrointestinal, renal and hepatic toxicity. Sensitivity to drug-associated adverse events varies with the individual patient. Dogs that have experienced adverse reactions from one NSAID may experience adverse reactions from another NSAID. Patients at greatest risk for renal toxicity are those that are dehydrated, on concomitant diuretic therapy, or those with existing renal, cardiovascular, and/or hepatic dysfunction. Concurrent administration of potentially nephrotoxic drugs should be carefully approached. NSAIDs may inhibit the prostaglandins that maintain normal homeostatic function. Such anti-prostaglandin effects may result in clinically significant disease in patients with underlying or pre-existing disease that has not been previously diagnosed. Since NSAIDs possess the potential to induce gastrointestinal ulcerations and/or perforations, concomitant use with other anti-inflammatory drugs, such as NSAIDs or corticosteroids, should be avoided. If additional pain medication is needed after administration of the total daily dose of Meloxicam Oral Suspension, a non-NSAID or non-corticosteroid class of analgesia should be considered. The use of another NSAID is not recommended. Consider appropriate washout times when switching from corticosteroid use or from one NSAID to another in dogs. The use of concomitantly protein-bound drugs with Meloxicam Oral Suspension has not been studied in dogs. Commonly used protein-bound drugs include cardiac, anticonvulsant and behavioral medications. The influence of concomitant drugs that may inhibit metabolism of Meloxicam Oral Suspension has not been evaluated. Drug compatibility should be monitored in patients requiring adjunctive therapy.

Adverse Reactions:

Field safety was evaluated in 306 dogs. Based on the results of two studies, GI abnormalities (vomiting, soft stools, diarrhea, and inappetence) were the most common adverse reactions associated with the administration of meloxicam. The following table lists adverse reactions and the numbers of dogs that experienced them during the studies. Dogs may have experienced more than one episode of the adverse reaction during the study.

Adverse Reactions Observed During Two Field Studies
Clinical Observation | Meloxicam (n=157) | Placebo (n=149)
Vomiting | 40 | 23
Diarrhea/Soft Stool | 19 | 11
Bloody Stool | 1 | 0
In appetence | 5 | 1
Bleeding gums after dental procedure | 1 | 0
Lethargy/Swollen Carpus | 1 | 0
Epiphora | 1 | 0

In foreign suspected adverse drug reaction (SADR) reporting over a 9 year period, incidences of adverse reactions related to meloxicam administration included: auto-immune hemolytic anemia (1 dog), thrombocytopenia (1 dog), polyarthritis (1 dog), nursing puppy lethargy (1 dog), and pyoderma (1 dog).

Post-Approval Experience (Rev. 2010):

The following adverse events are based on post-approval adverse drug experience reporting. Not all adverse reactions are reported to FDA/CVM. It is not always possible to reliably estimate the adverse event frequency or establish a causal relationship to product exposure using these data. The following adverse events are listed in decreasing order of frequency by body system.

Gastrointestinal: vomiting, anorexia, diarrhea, melena, gastrointestinal ulceration

Urinary: azotemia, elevated creatinine, renal failure

Neurological/Behavioral: lethargy, depression

Hepatic: elevated liver enzymes

Dermatologic: pruritus

Death has been reported as an outcome of the adverse events listed above. Acute renal failure and death have been associated with use of meloxicam in cats.

Contact Information:

To report suspected adverse experiences, for technical assistance or to obtain a copy of the Safety Data Sheet (SDS), contact Felix Pharmaceuticals Private Limited at 1-833-571-1525. For additional information about adverse drug experience reporting for animal drugs, contact FDA at 1-888-FDA-VETS or http://www.fda.gov/reportanimalae

Information for Dog Owners:

Meloxicam Oral Suspension, like other drugs of its class, is not free from adverse reactions. Owners should be advised of the potential for adverse reactions and be informed of the clinical signs associated with drug intolerance. Adverse reactions may include vomiting, diarrhea, decreased appetite, dark or tarry stools, increased water consumption, increased urination, pale gums due to anemia, yellowing of gums, skin or white of the eye due to jaundice, lethargy, incoordination, seizure, or behavioral changes. Serious adverse reactions associated with this drug class can occur without warning and in rare situations result in death (see Adverse Reactions). Owners should be advised to discontinue Meloxicam Oral Suspension and contact their veterinarian immediately if signs of intolerance are observed. The vast majority of patients with drug related adverse reactions have recovered when the signs are recognized, the drug is withdrawn, and veterinary care, if appropriate, is initiated. Owners should be advised of the importance of periodic follow up for all dogs during administration of any NSAID.

Clinical Pharmacology:

Meloxicam has nearly 100% bioavailability when administered orally with food. The terminal elimination half life after a single dose is estimated to be approximately 24 hrs (+/-30%) regardless of route of administration. There is no evidence of statistically significant gender differences in drug pharmacokinetics. Drug bioavailability, volume of distribution, and total systemic clearance remain constant up to 5 times the recommended dose for use in dogs. However, there is some evidence of enhanced drug accumulation and terminal elimination half-life prolongation when dogs are dosed for 45 days or longer.

Peak drug concentrations can be expected to occur within about 7.5 hrs after oral administration. Corresponding peak concentration is approximately 0.464 mcg/mL following a 0.2 mg/kg oral dose. The drug is 97% bound to canine plasma proteins.

Effectiveness:

The effectiveness of meloxicam was demonstrated in two field studies involving a total of 277 dogs representing various breeds, between six months and sixteen years of age, all diagnosed with osteoarthritis. Both of the placebo-controlled, masked studies were conducted for 14 days. All dogs received 0.2 mg/kg on day 1. All dogs were maintained on 0.1 mg/kg oral meloxicam from days 2 through 14 of both studies. Parameters evaluated by veterinarians included lameness, weight-bearing, pain on palpation, and overall improvement. Parameters assessed by owners included mobility, ability to rise, limping, and overall improvement. In the first field study (n=109), dogs showed clinical improvement with statistical significance after 14 days of meloxicam treatment for all parameters. In the second field study (n=48), dogs receiving meloxicam showed a clinical improvement after 14 days of therapy for all parameters; however, statistical significance was demonstrated only for the overall investigator evaluation on day 7, and for the owner evaluation on day 14.

Safety:

Six Week Study

In a six week target animal safety study, meloxicam was administered orally at 1, 3, and 5X the recommended dose with no significant clinical adverse reactions. Animals in all dose groups (control, 1, 3 and 5X the recommended dose) exhibited some gastrointestinal distress (diarrhea and vomiting). No treatment-related changes were observed in hematological, blood chemistry, urinalysis, clotting time, or buccal mucosal bleeding times. Necropsy results included stomach mucosal petechiae in one control dog, two dogs at the 3X and one dog at the 5X dose. Other macroscopic changes included areas of congestion or depression of the mucosa of the jejunum or ileum in three dogs at the 1X dose and in two dogs at the 5X dose. Similar changes were also seen in two dogs in the control group. There were no macroscopic small intestinal lesions observed in dogs receiving the 3X dose. Renal enlargement was reported during the necropsy of two dogs receiving the 3X dose and two receiving the 5X dose.

Microscopic examination of the kidneys revealed minimal degeneration or slight necrosis at the tip of the papilla in three dogs at the 5X dose. Microscopic examination of the stomach showed inflammatory mucosal lesions, epithelial regenerative hyperplasia or atrophy, and submucosal gland inflamation in two dogs at the recommended dose, three dogs at the 3X and four dogs at the 5X dose. Small intestinal microscopic changes included minimal focal mucosal erosion affecting the villi, and were sometimes associated with mucosal congestion. These lesions were observed in the ileum of one control dog and in the jejunum of one dog at the recommended dose and two dogs at the 5X dose.

Six Month Study

In a six month target animal safety study, meloxicam was administered orally at 1, 3, and 5X the recommended dose with no significant clinical adverse reactions. All animals in all dose groups (controls, 1, 3, and 5X the recommended dose) exhibited some gastrointestinal distress (diarrhea and vomiting). Treatment related changes seen in hematology and chemistry included decreased red blood cell counts in seven of 24 dogs (four 3X and three 5X dogs), decreased hematocrit in 18 of 24 dogs (including three control dogs), dose-related neutrophilia in one 1X, two 3X and three 5X dogs, evidence of regenerative anemia in two 3X and one 5X dog. Also noted were increased BUN in two 5X dogs and decreased albumin in one 5X dog. Endoscopic changes consisted of reddening of the gastric mucosal surface covering less than 25% of the surface area. This was seen in three dogs at the recommended dose, three dogs at the 3X dose and two dogs at the 5X dose. Two control dogs exhibited reddening in conjunction with ulceration of the mucosa covering less than 25% of the surface area.

Gross gastrointestinal necropsy results observed included mild discoloration of the stomach or duodenum in one dog at the 3X and in one dog at the 5X dose. Multifocal pinpoint red foci were observed in the gastric fundic mucosa in one dog at the recommended dose, and in one dog at the 5X dose.

No macroscopic or microscopic renal changes were observed in any dogs receiving meloxicam in this six month study. Microscopic gastrointestinal findings were limited to one dog at the recommended dose, and two dogs at the 3X dose. Mild inflammatory mucosal infiltrate was observed in the duodenum of one dog at the recommended dose. Mild congestion of the fundic mucosa and mild myositis of the outer mural musculature of the stomach were observed in two dogs receiving the 3X dose.

How Supplied:

Meloxicam Oral Suspension 1.5 mg/mL is supplied in 32 mL NDC 86101-067-52 and 100 mL NDC 86101-067-53 bottles with measuring syringe (1 mL and 5 mL).

Storage:

Store at controlled room temperature 68°F-77°F (20°C-25°C), excursions permitted between 59°F and 86°F (15°C and 30°C). Brief exposure to temperature up to 104°F (40°C) may be tolerated provided the mean kinetic temperature does not exceed 77°F (25°C); however such exposure should be minimized.

Approved by FDA under ANADA # 200-817

Distributed by:

Felixvet Inc.,
1300 NW Briarcliff Parkway,
Suite 100, Kansas City, Missouri 64150

Manufactured in India

Rev. July 2025

Client Information Sheet

Meloxicam Oral Suspension
1.5 mg/mL

Non-steroidal anti-inflammatory drug for oral use in dogs only

This summary contains important information about Meloxicam Oral Suspension. You should read this information before you start giving your dog Meloxicam Oral Suspension and review it each time the prescription is refilled. This sheet is provided only as a summary and does not take the place of instructions from your veterinarian. Talk to your veterinarian if you do not understand any of this information or if you want to know more about Meloxicam Oral Suspension.

What Is Meloxicam Oral Suspension?

Meloxicam Oral Suspension is a prescription non-steroidal anti-inflammatory drug (NSAID) that is used to control pain and inflammation (soreness) due to osteoarthritis in dogs. Osteoarthritis (OA) is a painful condition caused by "wear and tear" of cartilage and other parts of the joints that may result in the following changes or signs in your dog: Limping or lameness, decreased activity or exercise (reluctance to stand, climb stairs, jump or run, or difficulty in performing these activities), stiffness or decreased movement of joints. Meloxicam Oral Suspension is given to dogs by mouth. Do not use Meloxicam Oral Suspension in cats. Acute renal failure and death have been associated with the use of meloxicam in cats.

What Kind Of Results Can I Expect When My Dog Is On Meloxicam Oral Suspension For OA?

While Meloxicam Oral Suspension is not a cure for osteoarthritis, it can control the pain and inflammation of OA and improve your dog's mobility.

- Response varies from dog to dog but can be quite dramatic.
- In most dogs, improvement can be seen in a matter of days.
- If Meloxicam Oral Suspension is discontinued or not given as directed, your dog's pain and inflammation may come back.

What Dogs Should Not Take Meloxicam Oral Suspension?

Your dog should not be given Meloxicam Oral Suspension if he/she:

- Has had an allergic reaction to meloxicam, the active ingredient of Meloxicam Oral Suspension.
- Has had an allergic reaction (such as hives, facial swelling, or red or itchy skin) to aspirin or other NSAIDs
- Is presently taking aspirin, other NSAIDs, or corticosteroids (unless directed by your veterinarian).

Meloxicam Oral Suspension Should Only Be Given To Dogs

People should not take Meloxicam Oral Suspension. Keep Meloxicam Oral Suspension and all medication out of reach of children. Call your physician immediately if you accidentally take Meloxicam Oral Suspension.

How To Give Meloxicam Oral Suspension To Your Dog.

The actual dose to be given should be prescribed by the veterinarian.

Directions for Administration:

Dogs under 10 pounds (4.5 kg)

Shake well before use, then remove cap. Particular care should be given with regard to the accuracy of dosing.

To prevent accidental overdosing of small dogs, administer drops on food only, never directly into the mouth.

Carefully measure suspension onto food to assure that the correct dose is given before presentation of the food to the dog. The syringe provided with the meloxicam concentration of 1.5 mg/mL cannot be used to measure doses for dogs weighing less than 5 lbs (2.3 kg).

For dogs less than 5 lbs (2.3 kg), Meloxicam Oral Suspension can be given using the dropper bottle: one drop for each pound of body weight for the 1.5 mg/mL concentration (two drops for each kilogram of body weight), dropped directly onto the food.

For dogs between 5-10 pounds, Meloxicam Oral Suspension can be given by drops or by using the measuring syringe provided in the package (see dosing procedure below). The syringe fits on to the bottle and has a scale beginning at 5 lbs, designed to deliver the daily maintenance dose (0.05 mg/lb or 0.1 mg/kg). When using the syringe, the dog's weight should be rounded down to the nearest 5 pound increment. Replace and tighten cap after use.

Dogs over 10 pounds (4.5 kg)

Shake well before use then remove cap. Meloxicam Oral Suspension may be either mixed with food or placed directly into the mouth. Particular care should be given with regard to the accuracy of dosing. Meloxicam Oral Suspension can be given using the measuring syringe provided in the package (see dosing procedure below). The syringe fits on to the bottle and has a scale in pounds designed to deliver the daily maintenance dose (0.05 mg/lb or 0.1 mg/kg). When using the syringe, the dog's weight should be rounded down to the nearest 5 pound increment. Alternatively, Meloxicam Oral Suspension can be given using the dropper bottle: one drop for each pound of body weight for the 1.5 mg/mL concentration (two drops for each kilogram of body weight). Replace and tighten cap after use.

What To Tell/Ask Your Veterinarian Before Giving Meloxicam Oral Suspension

Talk to your veterinarian about:

- The signs of OA you have observed (for example limping, stiffness).
- The importance of weight control and exercise in the management of OA.
- What tests might be done before Meloxicam Oral Suspension is prescribed.
- How often your dog may need to be examined by your veterinarian.
- The risks and benefits of using Meloxicam Oral Suspension.

Tell your veterinarian if your dog has ever had the following medical problems:

- Experienced side effects from Meloxicam Oral Suspension or other NSAIDs, such as aspirin
- Digestive upset (vomiting and/or diarrhea)
- Liver disease
- Kidney disease

Tell your veterinarian about:

- Any other medical problems or allergies that your dog has now or has had.
- All medicines that you are giving your dog or plan to give your dog, including those you can get without a prescription.

Tell your veterinarian if your dog is:

- Pregnant, nursing or if you plan to breed your dog.

What Are The Possible Side Effects That May Occur In My Dog During Meloxicam Oral Suspension Therapy?

Meloxicam Oral Suspension, like other drugs, may cause some side effects. Serious but rare side effects have been reported in dogs taking NSAIDs. Serious side effects can occur with or without warning and in rare situations result in death.

The most common NSAID-related side effects generally involve the stomach and liver or kidney problems. Look for the following side effects that can indicate your dog may be having a problem with Meloxicam Oral Suspension or may have another medical problem:

- Decrease or increase in appetite
- Vomiting
- Change in bowel movement (such as diarrhea, or black, tarry or bloody stools)
- Change in behavior (such as decreased or increased activity level, incoordination, seizure or aggression)
- Yellowing of gums, skin, or whites of the eyes (jaundice)
- Change in drinking habits (frequency, amount consumed)
- Change in urination habits (frequency, color, or smell)
- Change in skin (redness, scabs, or scratching)

It is important to stop therapy and contact your veterinarian immediately if you think your dog has a medical problem or side effect from Meloxicam Oral Suspension therapy. If you have additional questions about possible side effects, talk to your veterinarian.

Can Meloxicam Oral Suspension Be Given With Other Medicines?

Meloxicam Oral Suspension should not be given with other NSAIDs (for example, aspirin, carprofen, etodolac, deracoxib) or steroids (for example, cortisone, prednisone, dexamethasone, triamcinolone).

Tell your veterinarian about all medicines you have given your dog in the past, and any medicines that you are planning to give with Meloxicam Oral Suspension. This should include other medicines that you can get without a prescription.

Your veterinarian may want to check that all of your dog's medicines can be given together.

What Can I Do In Case My Dog Eats More Than The Prescribed Amount?

Contact your veterinarian immediately if your dog eats more than the prescribed amount of Meloxicam Oral Suspension.

What Else Should I Know About Meloxicam Oral Suspension?

This sheet provides a summary of information about Meloxicam Oral Suspension. If you have any questions or concerns about Meloxicam Oral Suspension or osteoarthritis pain, talk to your veterinarian.

As with all prescribed medicines, Meloxicam Oral Suspension should only be given to the dog for which it was prescribed. Meloxicam Oral Suspension is for use in dogs only. Do not give Meloxicam Oral Suspension to cats. It should be given to your dog only for the condition for which it was prescribed. It is important to periodically discuss your dog's response to Meloxicam Oral Suspension at regular check ups. Your veterinarian will best determine if your dog is responding as expected and if your dog should continue receiving Meloxicam Oral Suspension.

To report suspected adverse experiences, for technical assistance or to obtain a copy of the Safety Data Sheet (SDS), contact Felix Pharmaceuticals Private Limited at 1-833-571-1525. For additional information about adverse drug experience reporting for animal drugs, contact FDA at 1-888-FDA-VETS or http://www.fda.gov/reportanimalae

Distributed by:
Felixvet Inc.,
1300 NW Briarcliff Parkway,
Suite 100, Kansas City, Missouri 64150

Manufactured in India

Rev. July 2025

PACKAGE LABEL.PRINCIPAL DISPLAY PANEL

NDC: 86101-067-52

Meloxicam Oral Suspension

1.5 mg/mL

Caution: Federal law restricts this drug to use by or on the order of a licensed veterinarian.

Non-steroidal anti-inflammatory drug for oral use in dogs only

Net Contents: 32 mL

Approved by FDA under ANADA # 200-817

PACKAGE LABEL.PRINCIPAL DISPLAY PANEL

NDC: 86101-067-53

Meloxicam Oral Suspension

1.5 mg/mL

Caution: Federal law restricts this drug to use by or on the order of a licensed veterinarian.

Non-steroidal anti-inflammatory drug for oral use in dogs only

Net Contents: 100 mL

Approved by FDA under ANADA # 200-817

PACKAGE LABEL.PRINCIPAL DISPLAY PANEL

NDC: 86101-067-52

Meloxicam Oral Suspension

1.5 mg/mL

Non-steroidal anti-inflammatory drug for oral use in dogs only

Caution: Federal law restricts this drug to use by or on the order of a licensed veterinarian.

Net Contents: 32 mL

Approved by FDA under ANADA # 200-817

PACKAGE LABEL.PRINCIPAL DISPLAY PANEL

NDC: 86101-067-53

Meloxicam Oral Suspension

1.5 mg/mL

Non-steroidal anti-inflammatory drug for oral use in dogs only

Caution: Federal law restricts this drug to use by or on the order of a licensed veterinarian.

Net Contents: 100 mL

Approved by FDA under ANADA # 200-817